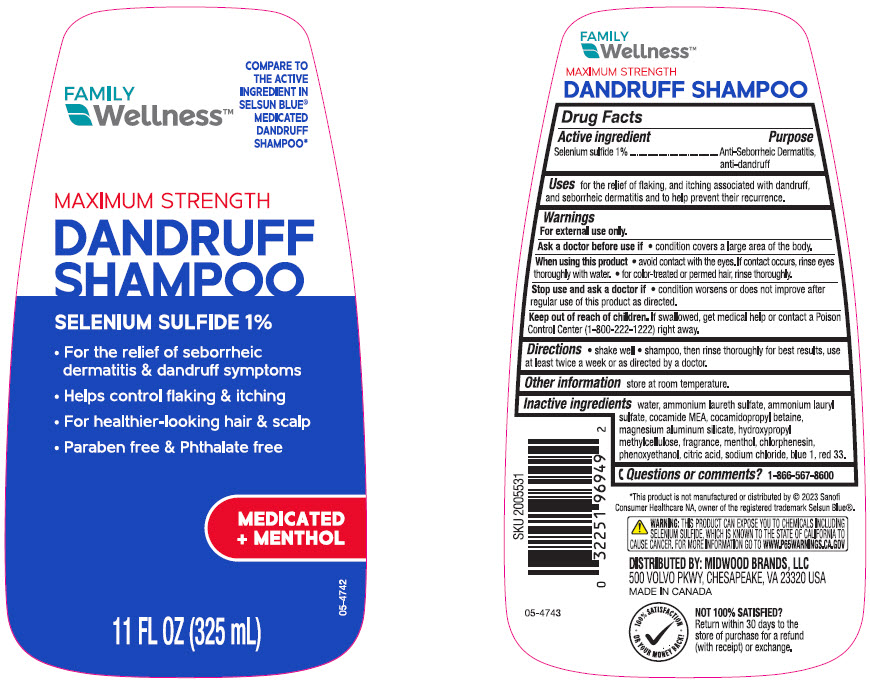 DRUG LABEL: FAMILY Wellness MAXIMUM STRENGTH DANDRUFF
NDC: 55319-949 | Form: SHAMPOO
Manufacturer: FAMILY DOLLAR SERVICES INC
Category: otc | Type: HUMAN OTC DRUG LABEL
Date: 20241021

ACTIVE INGREDIENTS: SELENIUM SULFIDE 10 mg/1 mL
INACTIVE INGREDIENTS: Water; AMMONIUM LAURETH-5 SULFATE; Ammonium Lauryl Sulfate; COCO MONOETHANOLAMIDE; Cocamidopropyl Betaine; Magnesium Aluminum Silicate; HYPROMELLOSE, UNSPECIFIED; MENTHOL, UNSPECIFIED FORM; Chlorphenesin; Phenoxyethanol; CITRIC ACID MONOHYDRATE; Sodium Chloride; FD&C BLUE NO. 1; D&C RED NO. 33

FAMILY Wellness™ MAXIMUM STRENGTH DANDRUFF SHAMPOO
Anti-dandruff, anti-seborrheic dermatitis, anti-psoriasis

Drug Facts

Active ingredient

Selenium sulfide 1%

Purpose

Anti-Seborrheic Dermatitis, anti-dandruff

Uses

for the relief of flaking, and itching associated with dandruff, and seborrheic dermatitis and to help prevent recurrence.

Warnings

For external use only.

Ask a doctor before use if

- condition covers a large area of the body.

When using this product

- avoid contact with the eyes. If contact occurs, rinse eyes thoroughly with water.
- for color-treated or permed hair, rinse thoroughly.

Stop use and ask a doctor if

- condition worsens or does not improve after regular use of this product as directed.

Keep out of reach of children. If swallowed, get medical help or contact a Poison Control Center right away.

Directions

- shake well
- shampoo, then rinse thoroughly
- for best results, use at least twice a week or as directed by a doctor.

Other information

- store at room temperature

Inactive ingredients

water, ammonium laureth sulfate, ammonium lauryl sulfate, cocamide MEA, cocamidopropyl betaine, magnesium aluminum silicate, hydroxypropyl methylcellulose, fragrance, menthol, chlorphenesin, phenoxyethanol, citric acid, sodium chloride, blue 1, red 33.

Questions or comments?

1-866-567-8600

DISTRIBUTED BY: MIDWOOD BRANDS, LLC
500 VOLVO PKWY, CHESAPEAKE, VA 23320 USA

PRINCIPAL DISPLAY PANEL - 325 mL Bottle Label

FAMILY
Wellness™

COMPARE TO
THE ACTIVE
INGREDIENT IN
SELSUN BLUE®
MEDICATED
DANDRUFF
SHAMPOO*

MAXIMUM STRENGTH

DANDRUFF
SHAMPOO

SELENIUM SULFIDE 1%

- For the relief of seborrheic
  dermatitis & dandruff symptoms
- Helps control flaking & itching
- For healthier-looking hair & scalp
- Paraben free & Phthalate free

MEDICATED
+ MENTHOL

11 FL OZ (325 mL)

05-4742